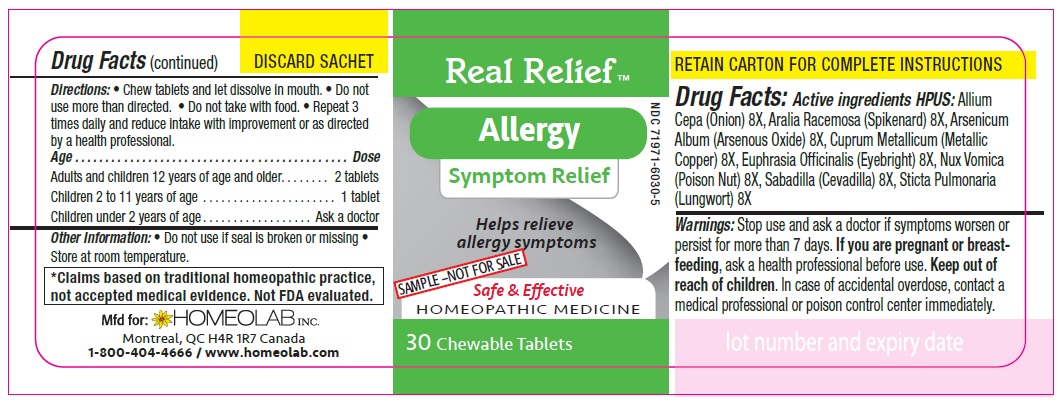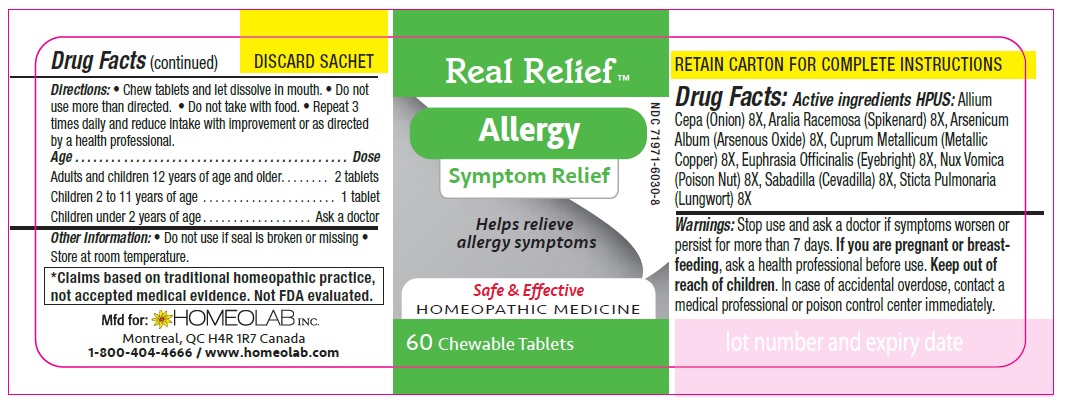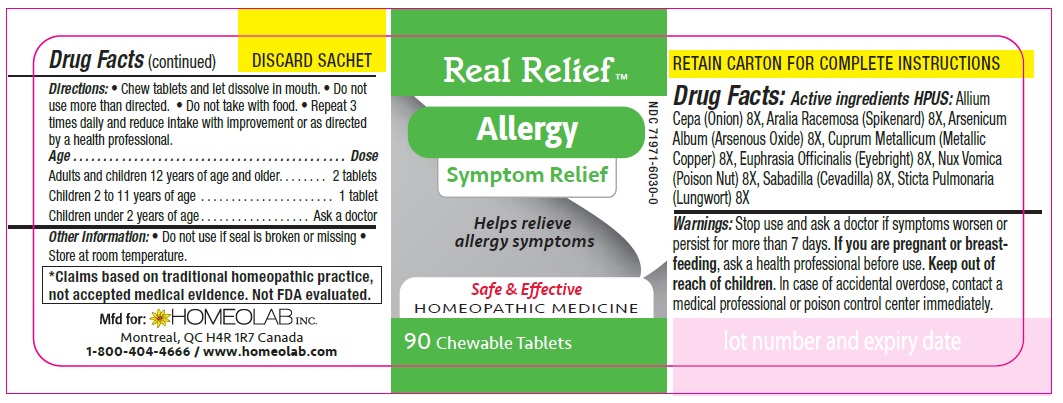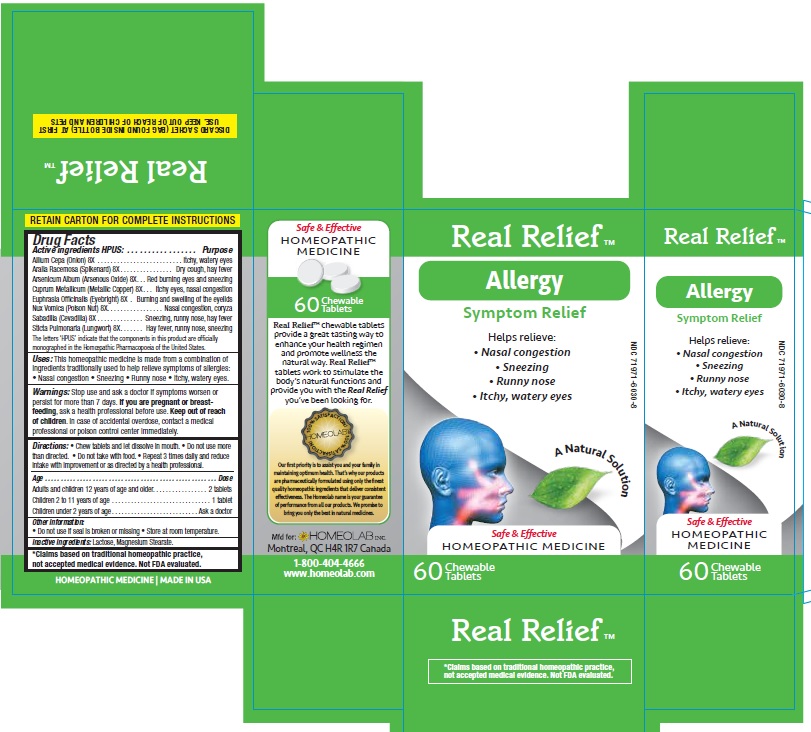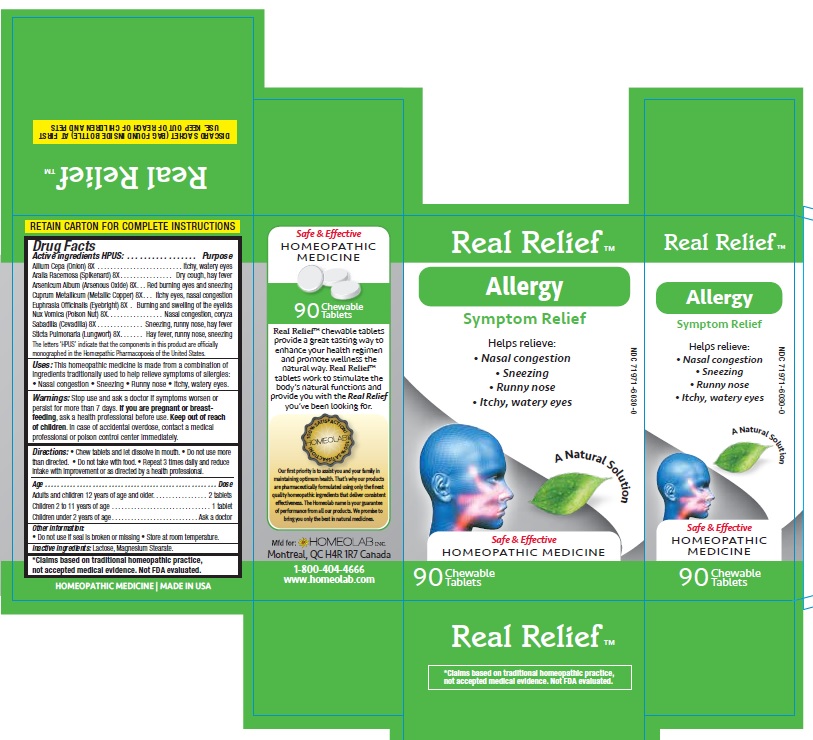 DRUG LABEL: Real Relief
NDC: 65808-318 | Form: TABLET
Manufacturer: GMP Laboratories of America, Inc.
Category: homeopathic | Type: HUMAN OTC DRUG LABEL
Date: 20201229

ACTIVE INGREDIENTS: ONION 8 [hp_X]/1 1; ARALIA RACEMOSA ROOT 8 [hp_X]/1 1; ARSENIC TRIOXIDE 8 [hp_X]/1 1; COPPER 8 [hp_X]/1 1; EUPHRASIA STRICTA 8 [hp_X]/1 1; STRYCHNOS NUX-VOMICA SEED 8 [hp_X]/1 1; SCHOENOCAULON OFFICINALE SEED 8 [hp_X]/1 1; LOBARIA PULMONARIA 8 [hp_X]/1 1
INACTIVE INGREDIENTS: LACTOSE MONOHYDRATE; MAGNESIUM STEARATE

Active Ingredients HPUS:

Allium cepa (Onion) 8 [hp-X]

Aralia racemosa (Spikenard) 8 [hp-X]

Arsenicum album (Arsenous trioxyde) 8 [hp-X]

Cuprum metallicum (Metallic copper) 8 [hp-X]

Euphrasia officinalis (Eyebright) 8 [hp-X]

Nux vomica (Poison nut) 8 [hp-X]

Sabadilla (Sabadilla) 8 [hp-X]

Sticta pulmonaria (Lungwort) 8 [hp-X]

Purpose

Homeopathic remedy helps relieve symptoms of all types of allergies:

- itchy, watery eyes
- red burning eyes and sneezing
- nasal congestion, coryza
- burning and swelling of the eye lids
- sneezing, runny nose, hay fever
- hay fever, sneezing, runny nose
- dry cough, hay fever
- itchy eyes, nasal congestion

The letters 'HPUS' indicate that the components in this product are officially monographed in the Homoeopathic Pharmacopoeia of the United States.

*Claims based on traditional homeopathic practice, not accepted medical evidence. Not FDA evaluated

Uses

This homeopathic remedy to relieve from symptoms of all allergies

- Nasal congestion
- Sneezing
- Runny nose
- Itchy, watery eyes

Warnings

Stop use and ask a doctor if symptoms worsen or last for more than 7 days.

If you are pregnant or breastfeeding, ask a health professional before use.

Keep out of reach of children.

In case of accidental overdose, contact a medical professional or poison control center immediately.

Directions

Chew tablets and let dissolve in mouth.

Do not use more than directed.

Do not take with food.

Repeat 3 times daily and reduce intake with improvement or as directed by a health professional

Age…………………………………………………………........ Dose

Adults and Children 12 years of age and older………...... 2 tablets

Children 2 to 11 years of age…...……………………............ 1 tablet

Children under 2 years of age……………………................. Ask a doctor

Other information

- Store at room temperature.
- Do not use if seal is broken or missing.

Inactive ingredients

Lactose, Magnesium Stearate.